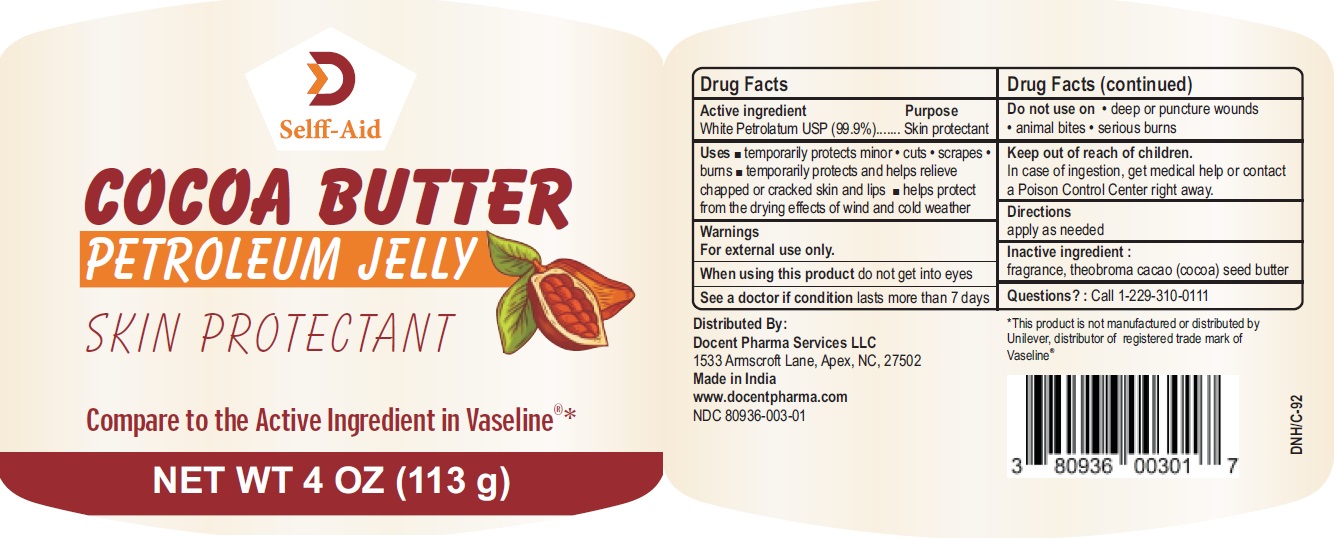 DRUG LABEL: Selff-Aid Cocoa Butter Petroleum Jelly
NDC: 80936-003 | Form: JELLY
Manufacturer: Docent Pharma Services, LLC
Category: otc | Type: HUMAN OTC DRUG LABEL
Date: 20210223

ACTIVE INGREDIENTS: PETROLATUM 99.9 g/100 g
INACTIVE INGREDIENTS: COCOA BUTTER

Selff-Aid Cocoa Butter Petroleum Jelly

Active Ingredient

White Petrolatum USP (99.9%)

Purpose

Skin protectant

Uses

- temporarily protects minor
  - cuts
  - scrapes
  - burns
- temporarily protects and helps relieve chapped or cracked skin and lips
- helps protect from the drying effects of wind and cold weather

Warnings

For external use only.

When using this product do not get into eyes

ASK DOCTOR

See a doctor if condition lasts more than 7 days

Do not use on

- deep or puncture wounds
- animal bites
- serious burns

Keep out of reach of children

In case of ingestion, get medical help or contact a Poison Control Center right away.

Directions

apply as needed

Inactive ingredients

fragrance, theobroma cacao (cocoa) seed butter

Questions?

Call 1-229-310-0111

Distributed By:
Docent Pharma Services, LLC
1533 Armscroft Lane, Apex, NC, 27502
Made in India
www.docentpharma.com

PACKAGE LABEL

PRINCIPAL DISPLAY PANEL

NDC 80936-003-01

Selff-Aid Cocoa Butter Petroleum Jelly

Skin Protectant

NET WT 4 OZ (113 g)